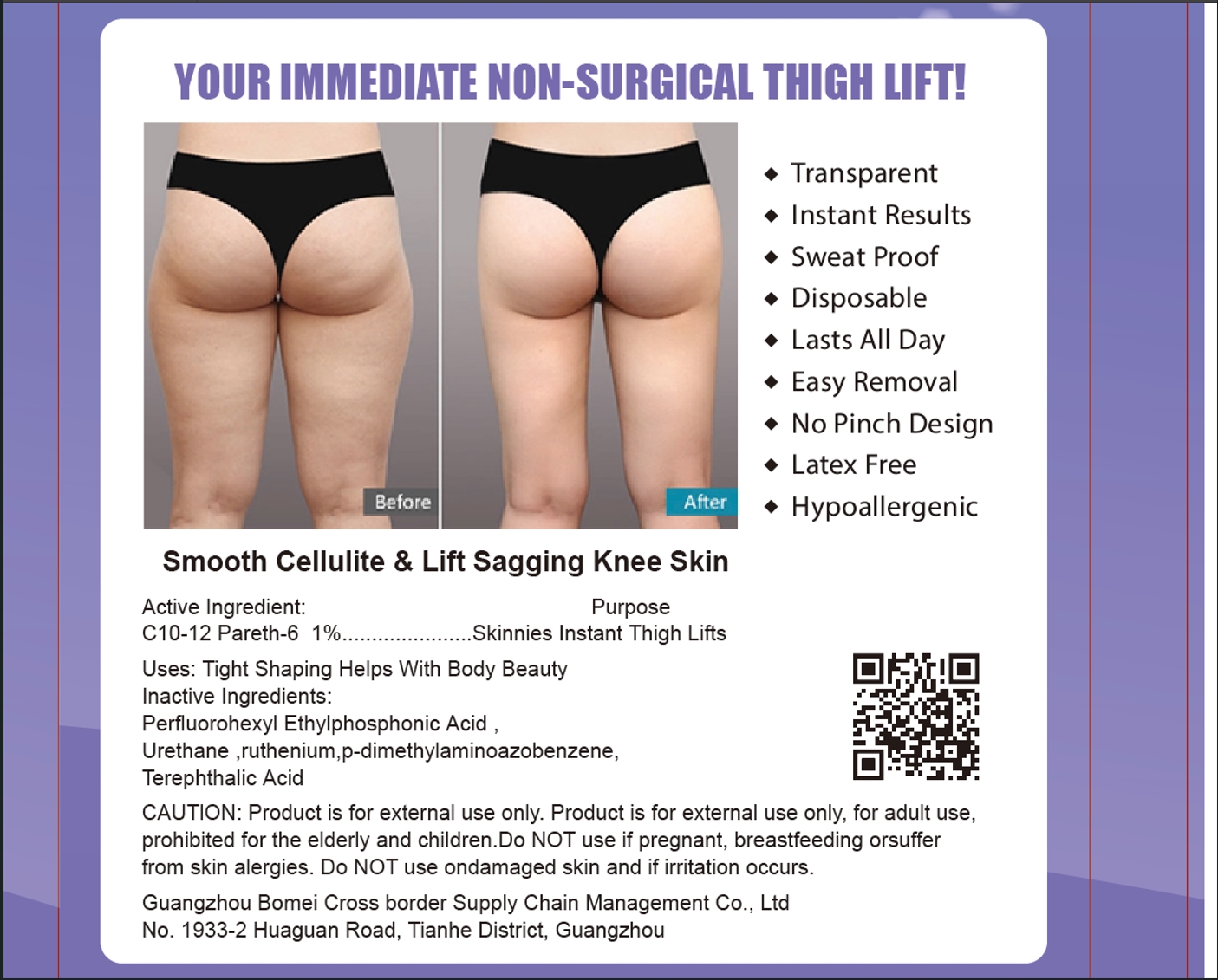 DRUG LABEL: INSTANT THIGH LIFTS
NDC: 84537-003 | Form: PATCH
Manufacturer: Guangzhou Bomei Cross border Supply Chain Management Co., Ltd
Category: homeopathic | Type: HUMAN OTC DRUG LABEL
Date: 20240807

ACTIVE INGREDIENTS: C10-12 PARETH-6 1 g/100 1
INACTIVE INGREDIENTS: TEREPHTHALIC ACID; URETHANE; P-DIMETHYLAMINOAZOBENZENE; PERFLUOROHEXYL ETHYLPHOSPHONIC ACID; RUTHENIUM

INSTANT THIGH LIFTS

ACTIVE INGREDIENT

C10-12 PARETH-6 1%

PURPOSE

Skinnies Instant Thigh Lifts

KEEP OUT OF REACH OF CHILDREN SECTION

INDICATIONS AND USAGE

Uses: Tight Shaping Helps With Body Beauty

WARNINGS

Product is for external use only. Product is for external use only, for adult useprohibited for the elderly and children.Do NOT use if pregnant, breastfeeding orsufferfrom skin alergies. Do NOT use ondamaged skin and if irritation occurs.

DOSAGE AND ADMINISTRATION

Smooth Cellulite & Lift sagging Knee Skin

INACTIVE INGREDIENT

PERFLUOROHEXYL ETHYLPHOSPHONIC ACID
URETHANE
RUTHENIUM
P-DIMETHYLAMINOAZOBENZENE
TEREPHTHALIC ACID